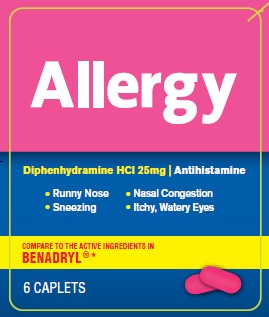 DRUG LABEL: Allergy
NDC: 29485-7007 | Form: TABLET
Manufacturer: Mechanical Servants, LLC
Category: otc | Type: HUMAN OTC DRUG LABEL
Date: 20211006

ACTIVE INGREDIENTS: DIPHENHYDRAMINE HYDROCHLORIDE 25 mg/1 1
INACTIVE INGREDIENTS: SILICON DIOXIDE; D&C RED NO. 27; ANHYDROUS DIBASIC CALCIUM PHOSPHATE; MAGNESIUM STEARATE; CELLULOSE, MICROCRYSTALLINE; POLYETHYLENE GLYCOL 400; STEARIC ACID; TITANIUM DIOXIDE; STARCH, CORN; POLYVINYL ALCOHOL, UNSPECIFIED; TALC

Allergy

Active ingredient

(in each caplet)

Diphenhydramine HCl (25 mg)

PURPOSE

Antihistamine

Warnings

Do not use

- to make a child sleepy
- with any other product containing Diphenhydramine, even one used on the skin

Ask a doctor before use if you have

- trouble urinating due to an enlarged prostate gland
- a breathing problem such as emphysema or chronic bronchitis
- glaucoma

Ask a doctor or pharmacist before use if you are

- taking sedatives or tranquilizers

When using this product

- avoid alcoholic drinks
- marked drowsiness may occur
- excitability may occur, especially in children
- alcohol, sedatives, and tranquilizers may increase drowsiness
- be careful when driving a motor vehicle or operating machinery

If pregnant or breast-feeding

ask a health professional before use

Keep out of the reach of children

In case of overdose, get medical help or contact a Poison Control Center right away.

Directions

- take every 4 to 6 hours, or as directed by a doctor
- do not take more than 6 doses in 24 hours

adults and children 12 years and over 1 to 2 tablets

children 6 to under 12 years 1 tablet

children under 6 years ask a doctor

Inactive ingredients

colloidal silicon dioxide, corn starch, D & C red # 27 Aluminum lake, dicalcium phosphate, magnesium stearate, microcrystalline cellulose, polyethylene glycol, polyvinyl alcohol, stearic acid, talc, titanium dioxide

Questions or comments?

Call 1-844-428-2538

Uses

Temporarily relieves these symptoms due to hay fever or other upper respiratory allergies

- sneezing
- nasal congestion
- runny nose
- itchy, watery eyes

Temporarily relieves these symptoms due to common cold

- runny nose
- sneezing

PACKAGE LABEL

ALLERGY

Diphenhydramine HCI 25mg | Antihistamine

Runny Nose Nasal Congestion

Sneezing Itchy Watery Eyes

COMPARE TO THE ACTIVE INGREDIENTS IN

BENADRYL® *

6 TABLETS